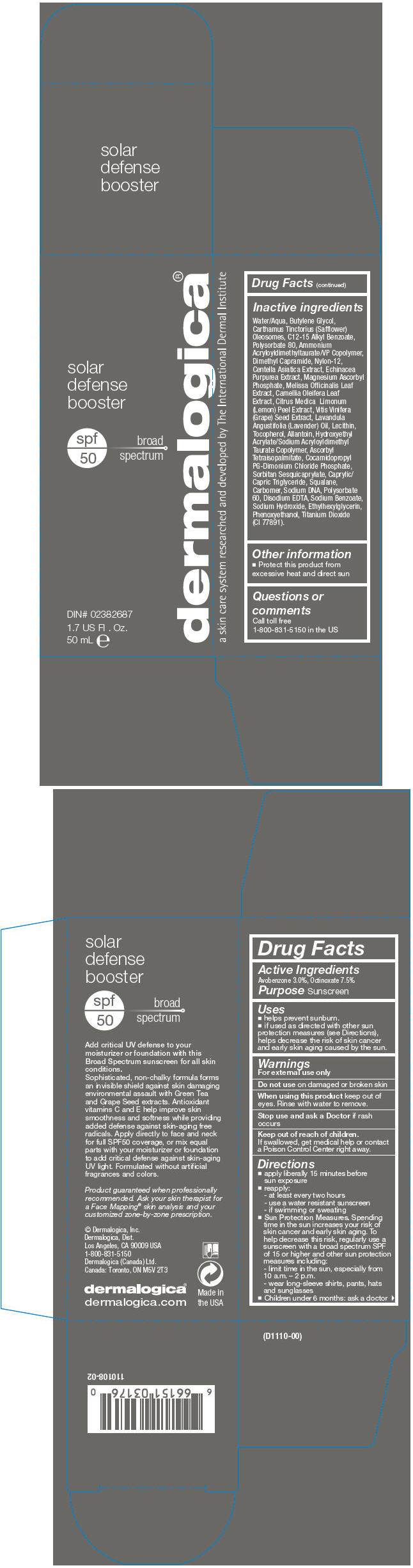 DRUG LABEL: Solar Defense Booster 
NDC: 68479-000 | Form: LOTION
Manufacturer: Dermalogica, Inc.
Category: otc | Type: HUMAN OTC DRUG LABEL
Date: 20131216

ACTIVE INGREDIENTS: Avobenzone 30 mg/1 mL; Octinoxate 70 mg/1 mL
INACTIVE INGREDIENTS: BUTYLENE GLYCOL; CARTHAMUS TINCTORIUS SEED OLEOSOMES; ALKYL (C12-15) BENZOATE; POLYSORBATE 80; AMMONIUM ACRYLOYLDIMETHYLTAURATE/VP COPOLYMER; DIMETHYL CAPRAMIDE; NYLON-12; CENTELLA ASIATICA; ECHINACEA PURPUREA; MAGNESIUM ASCORBYL PHOSPHATE; MELISSA OFFICINALIS LEAF; CAMELLIA OLEIFERA LEAF; LEMON PEEL; VITIS VINIFERA SEED; LAVENDER OIL; EGG PHOSPHOLIPIDS; TOCOPHEROL; ALLANTOIN; HYDROXYETHYL ACRYLATE/SODIUM ACRYLOYLDIMETHYL TAURATE COPOLYMER (45000 MPA.S AT 1%); ASCORBYL TETRAISOPALMITATE; COCAMIDOPROPYL PG-DIMONIUM CHLORIDE PHOSPHATE; SORBITAN SESQUIOLEATE; MEDIUM-CHAIN TRIGLYCERIDES; SQUALANE; CARBOMER HOMOPOLYMER TYPE C (ALLYL PENTAERYTHRITOL CROSSLINKED); HERRING SPERM DNA; POLYSORBATE 60; EDETATE DISODIUM; ETHYLHEXYLGLYCERIN; SODIUM HYDROXIDE; PHENOXYETHANOL; TITANIUM DIOXIDE

Solar Defense Booster
SPF50

Drug Facts

Active Ingredients

Avobenzone 3.0%, Octinoxate 7.5%

Purpose

Sunscreen

Uses

- helps prevent sunburn.
- if used as directed with other sun protection measures (see Directions), helps decrease the risk of skin cancer and early skin aging caused by the sun.

Warnings

For external use only

Do not use on damaged or broken skin

When using this product keep out of eyes. Rinse with water to remove.

Stop use and ask a Doctor if rash occurs

Keep out of reach of children.

If swallowed, get medical help or contact a Poison Control Center right away.

Directions

- apply liberally 15 minutes before sun exposure
- reapply:
  - at least every two hours
  - use a water resistant sunscreen
  - if swimming or sweating
- Sun Protection Measures. Spending time in the sun increases your risk of skin cancer and early skin aging. To help decrease this risk, regularly use a sunscreen with a broad spectrum SPF of 15 or higher and other sun protection measures including:
  - limit time in the sun, especially from 10 a.m. – 2 p.m.
  - wear long-sleeve shirts, pants, hats and sunglasses
- Children under 6 months: ask a doctor

Inactive ingredients

Water/Aqua, Butylene Glycol, Carthamus Tinctorius (Safflower) Oleosomes, C12-15 Alkyl Benzoate, Polysorbate 80, Ammonium Acryloyldimethyltaurate/VP Copolymer, Dimethyl Capramide, Nylon-12, Centella Asiatica Extract, Echinacea Purpurea Extract, Magnesium Ascorbyl Phosphate, Melissa Officinalis Leaf Extract, Camellia Oleifera Leaf Extract, Citrus Medica Limonum (Lemon) Peel Extract, Vitis Vinifera (Grape) Seed Extract, Lavandula Angustifolia (Lavender) Oil, Lecithin, Tocopherol, Allantoin, Hydroxyethyl Acrylate/Sodium Acryloyldimethyl Taurate Copolymer, Ascorbyl Tetraisopalmitate, Cocamidopropyl PG-Dimonium Chloride Phosphate, Sorbitan Sesquicaprylate, Caprylic/Capric Triglyceride, Squalane, Carbomer, Sodium DNA, Polysorbate 60, Disodium EDTA, Sodium Benzoate, Sodium Hydroxide, Ethylhexylglycerin, Phenoxyethanol, Titanium Dioxide (CI 77891).

Other information

- Protect this product from excessive heat and direct sun

Questions or comments

Call toll free
1-800-831-5150 in the US

PRINCIPAL DISPLAY PANEL - 50 mL Bottle Carton

solar
defense
booster

spf
50

broad
spectrum

DIN# 02382687

1.7 US Fl . Oz.
50 mL e

dermalogica®